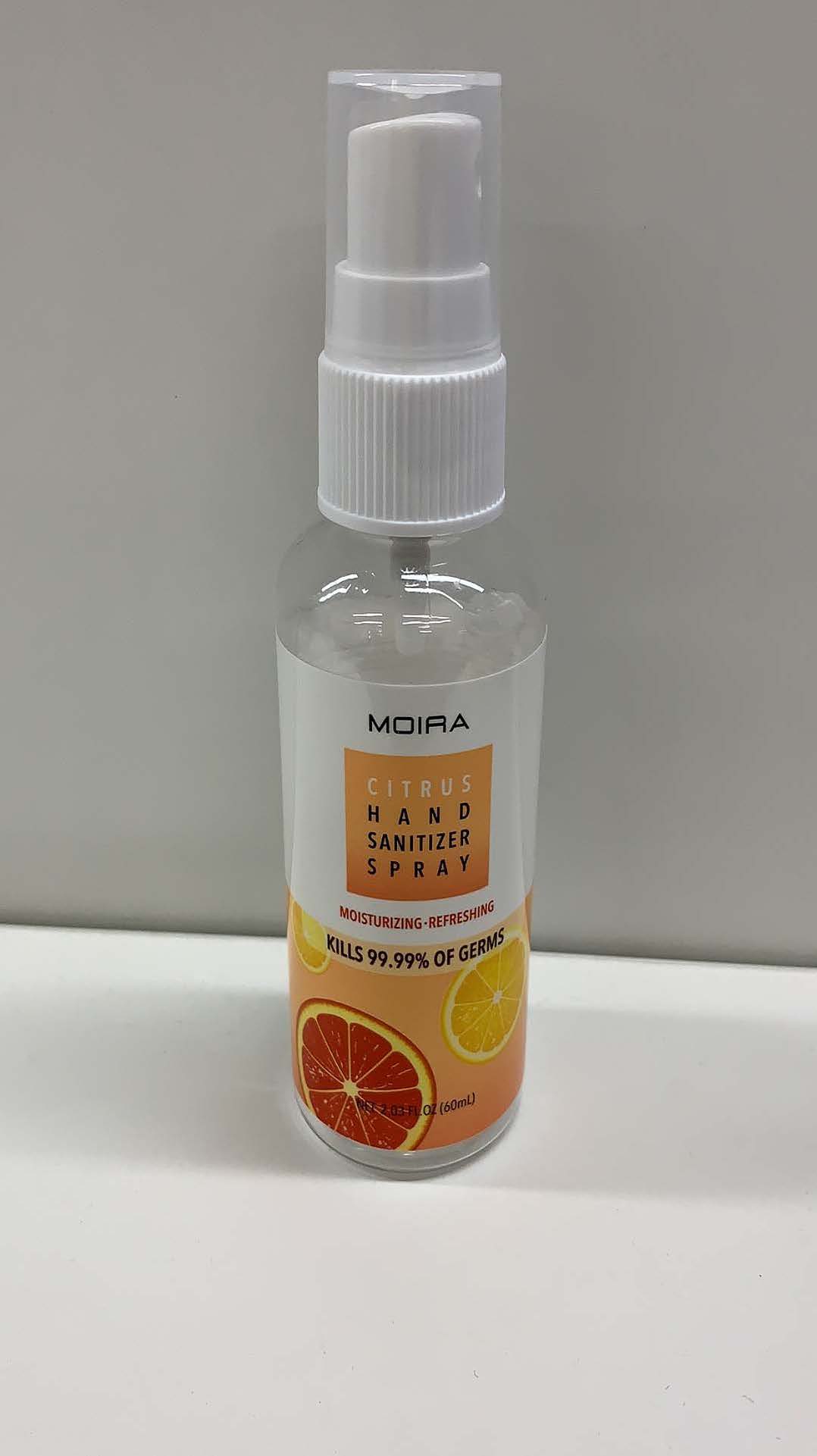 DRUG LABEL: MOIRA Hand Sanitizer
NDC: 79691-100 | Form: SPRAY
Manufacturer: Moira Cosmetics, Inc.
Category: otc | Type: HUMAN OTC DRUG LABEL
Date: 20200720

ACTIVE INGREDIENTS: ALCOHOL 75 mL/100 mL
INACTIVE INGREDIENTS: GLYCERIN; WATER; TOCOPHEROL

Active Ingredient(s)

Alcohol 75% v/v. Purpose: Antimicrobial

Purpose

Antimicrobial, Hand Sanitizer

Use

Hand sanitizer to help reduce bacteria on the skin.
Recommended for repeated use.

Warnings

For external use only. Flammable. Keep away from heat or flame

Do not use

- in children less than 2 months of age
- on open skin wounds

When using this product keep out of eyes, ears, and mouth. In case of contact with eyes, rinse eyes thoroughly with water.
Stop use and ask a doctor if irritation or rash occurs. These may be signs of a serious condition.
Keep out of reach of children. If swallowed, get medical help or contact a Poison Control Center right away.

Stop use and ask a doctor if irritation or rash occurs. These may be signs of a serious condition.

Keep out of reach of children. If swallowed, get medical help or contact a Poison Control Center right away.

Directions

- Place enough product on hands to cover all surfaces. Rub hands together until dry.
- For children under 6, use only under adult supervision.
- Not recommended for infants.

Other information

- Store between 15oC-30oC (59oF-86oF).
- Avoid freezing and excessive heat above 40oC (104oF).

Inactive ingredients

Water, Glycerin, Sodium Hyaluronate, Tocopherol, Citrus Limon (Lemon) Peel Oil, Citrus Paradisi (Grapefruit) Peel Oil, Linalool, Citral, Limonene.